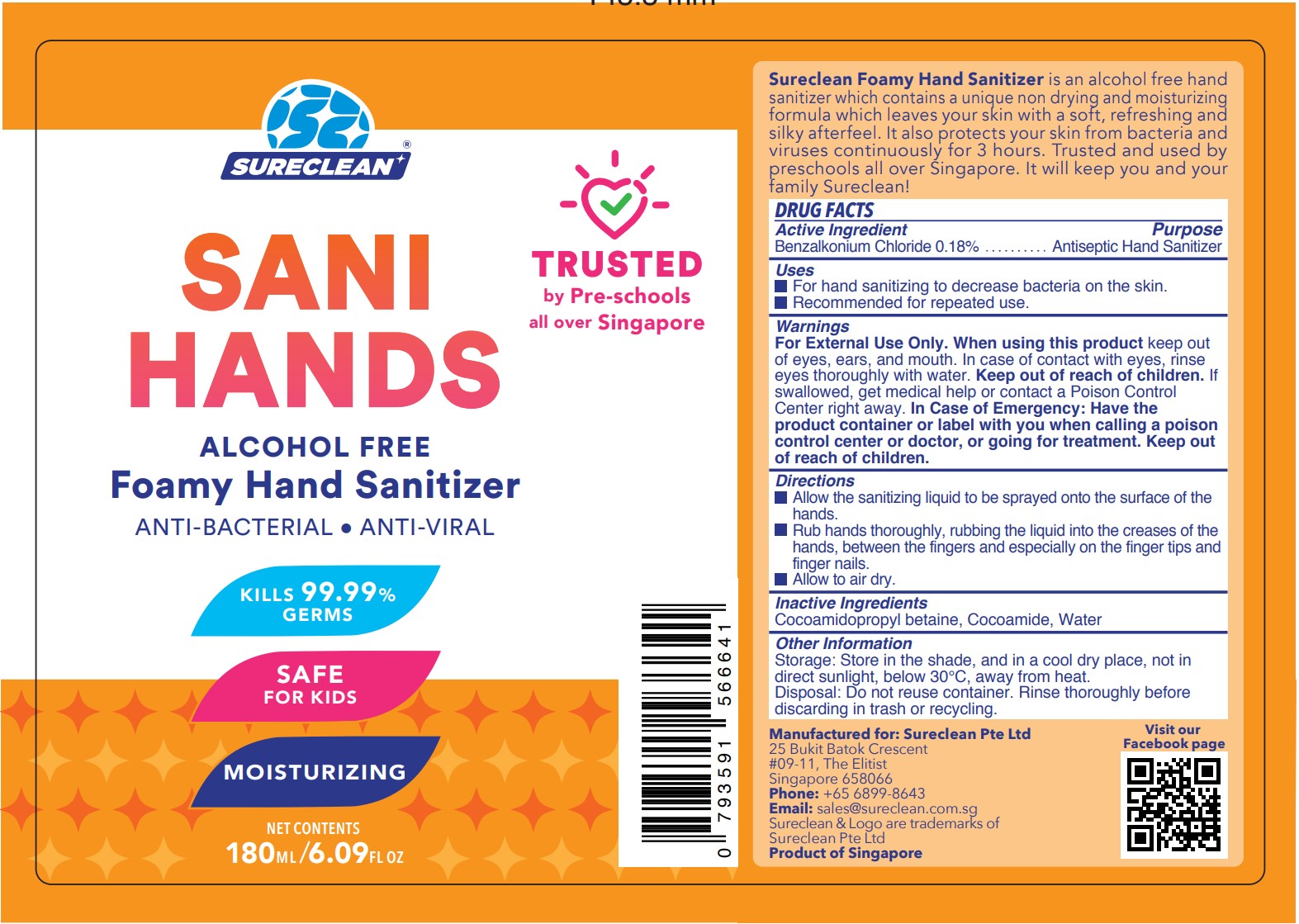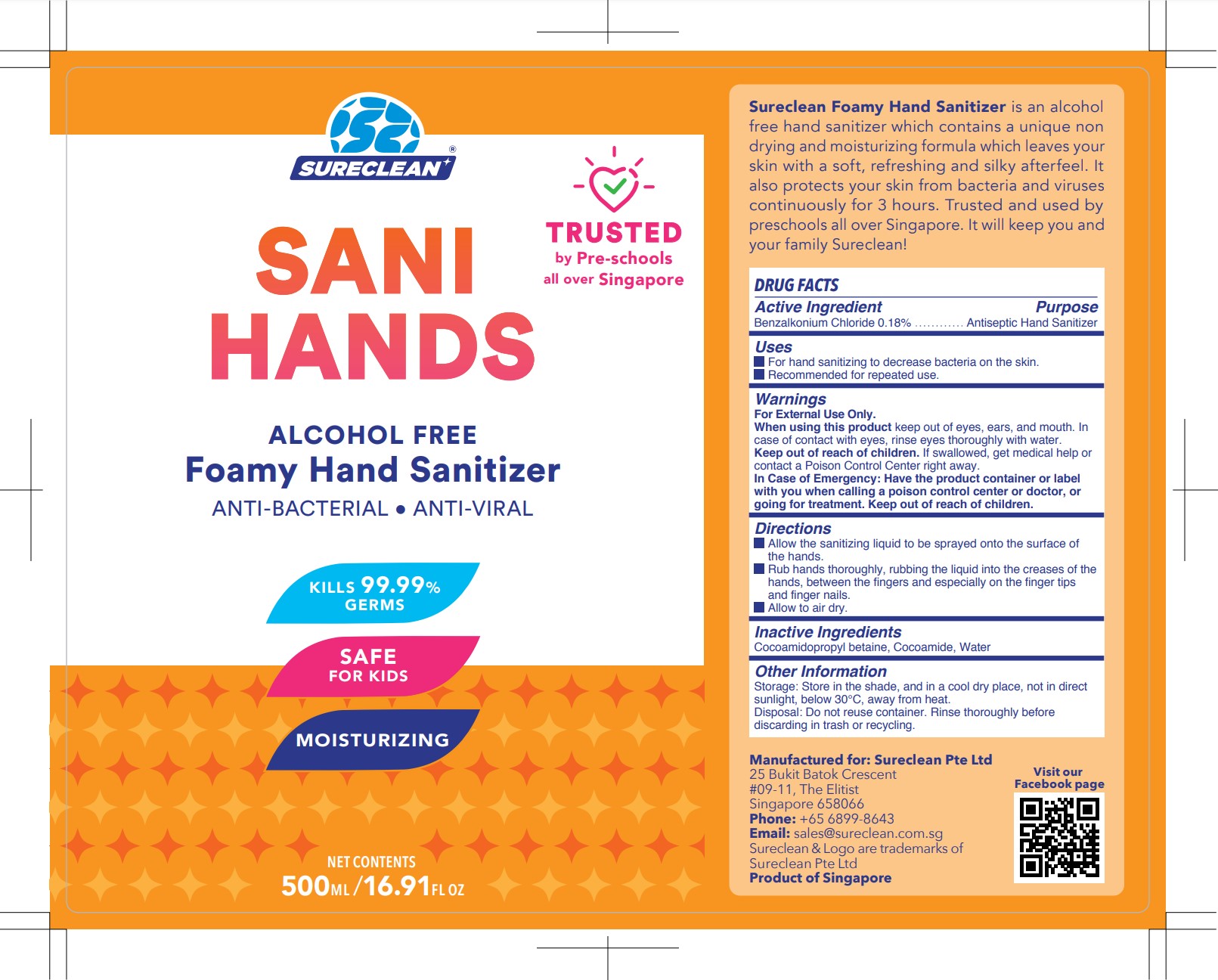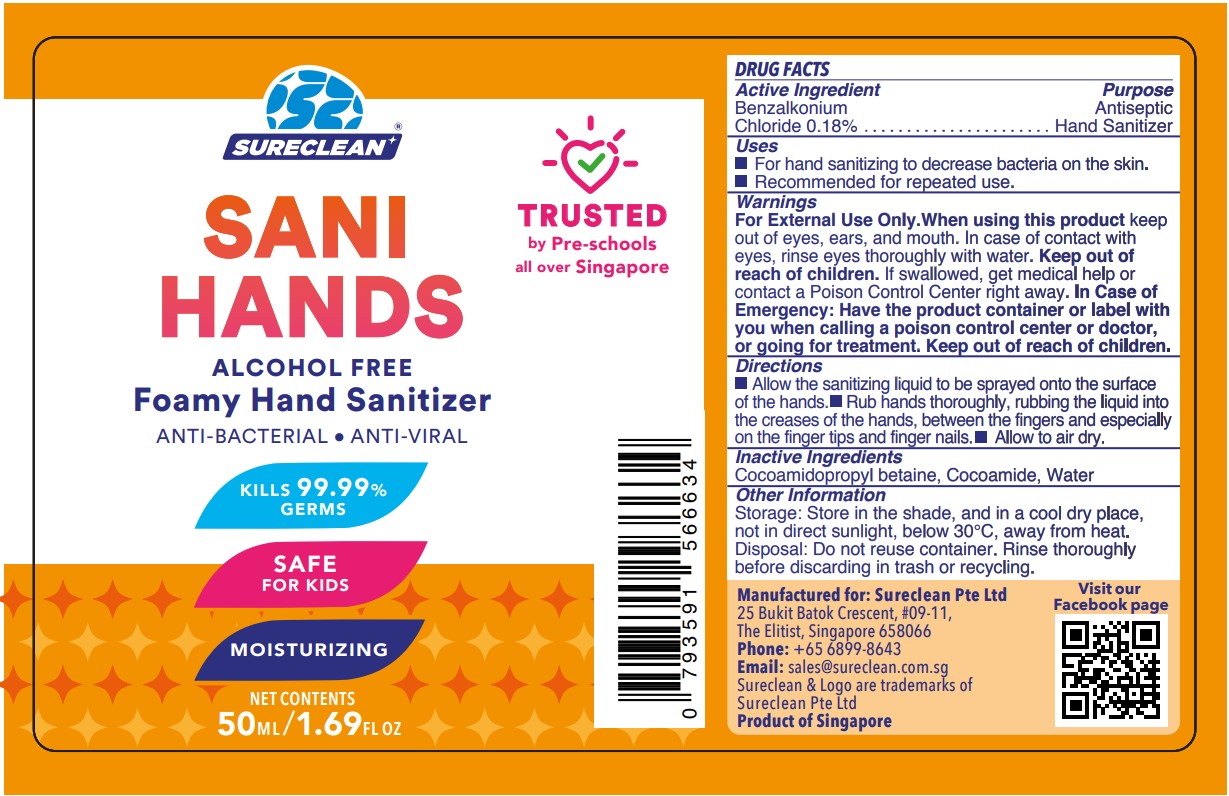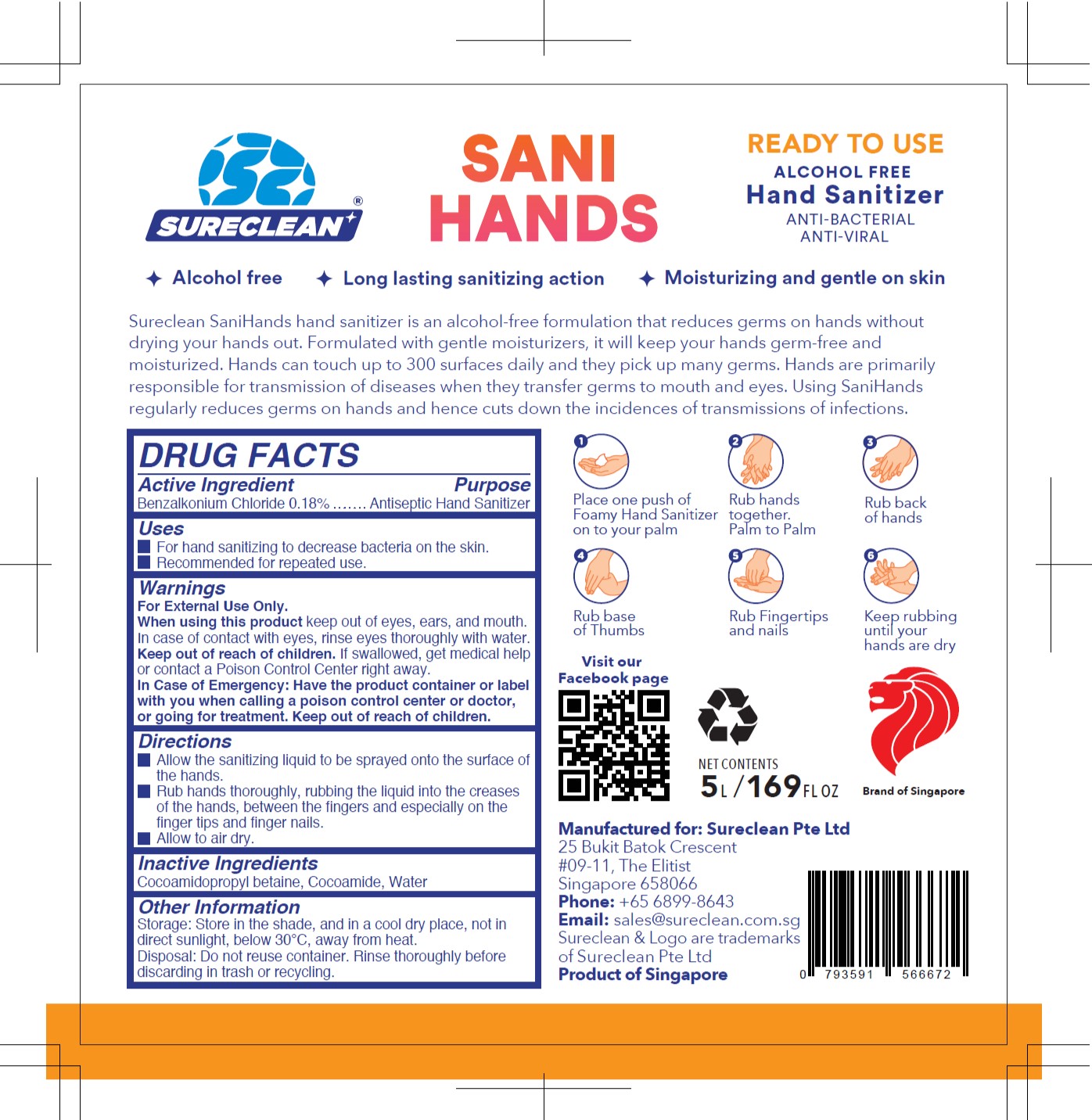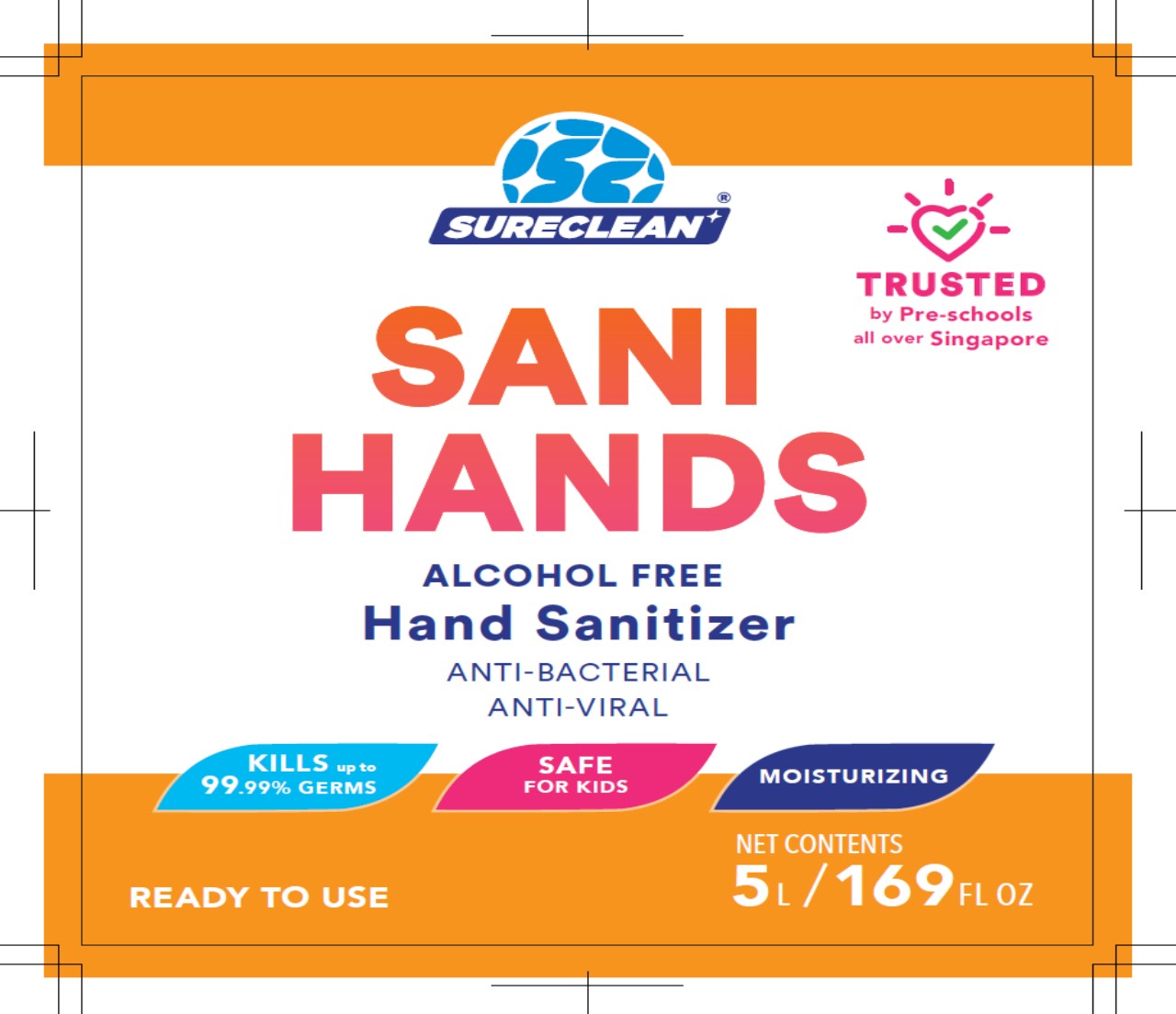 DRUG LABEL: Sanihands
NDC: 79211-218 | Form: LIQUID
Manufacturer: Porter Aerospace, LLC
Category: otc | Type: HUMAN OTC DRUG LABEL
Date: 20200616

ACTIVE INGREDIENTS: BENZALKONIUM CHLORIDE 0.18 g/100 mL
INACTIVE INGREDIENTS: COCAMIDOPROPYL BETAINE 3 g/100 mL; COCAMIDE 3 g/100 mL; WATER 93.82 mL/100 mL

SureClean Sanihands

ACTIVE INGREDIENT

Benzalkonium Chloride 0.18%

PURPOSE

Antimicrobial/Antiseptic Hand Sanitizer

INDICATIONS AND USAGE

- For hand sanitizing to decrease bacteria on the skin.
- Recommended for repeated use.

WARNINGS

For External Use Only

When using this product keep out of eyes, ears, and mouth. In case of contact with eyes, rinse eyes thoroughly with water

Keep out of reach of children. If swallowed, get medical help or contact a Poison Control Center right away.

In Case of Emergency: Have the product container or label with you when calling a poison control center or doctor, or going for treatment.

WHEN USING

For External Use Only

When using this product keep out of eyes, ears, and mouth. In case of contact with eyes, rinse eyes thoroughly with water

DOSAGE AND ADMINISTRATION

- Allow the sanitizing liquid to be sprayed onto the surface of the hands.
- Rub hands thoroughly, rubbing the liquid into the creases of the hands, between the fingers and especially on the finger
tips and finger nails.
- Allow to air dry.

STORAGE AND HANDLING

Storage:Store in the shade, and in a cool dry place, not in direct sunlight, below 30°C, away from heat.

Disposal: Do not reuse container. Rinse thoroughly before discarding in trash or recycling.

INACTIVE INGREDIENT

Cocoamidopropyl betaine, Cocoamide, Water

Keep out of reach of children. If swallowed, get medical help or contact a Poison Control Center right away.

PACKAGE LABEL

5000 mL / 169 FL OZ

Front

5L Back

500 mL

180 mL

50 mL